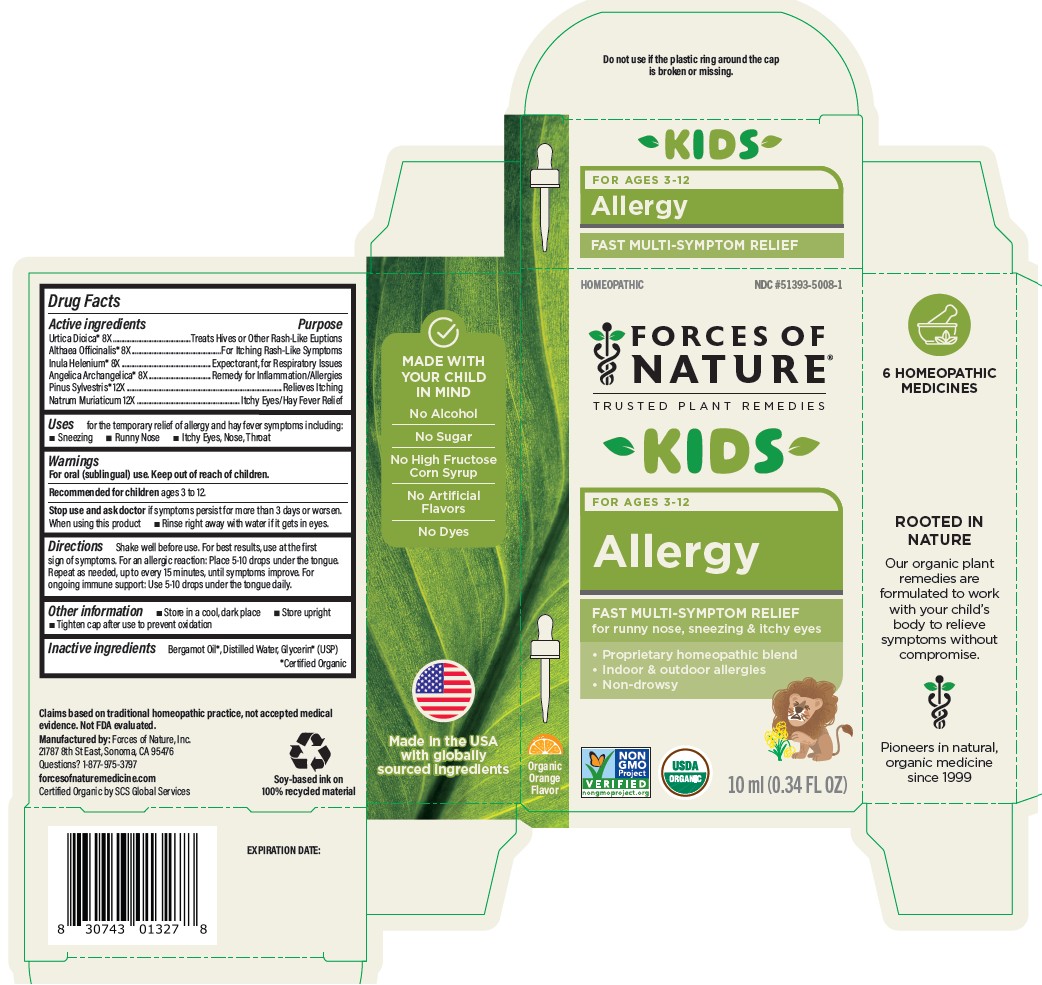 DRUG LABEL: Allergy Kids
NDC: 51393-5008 | Form: SOLUTION/ DROPS
Manufacturer: Forces of Nature
Category: homeopathic | Type: HUMAN OTC DRUG LABEL
Date: 20260220

ACTIVE INGREDIENTS: URTICA DIOICA LEAF 8 [hp_X]/100 mL; INULA HELENIUM ROOT 8 [hp_X]/100 mL; ANGELICA ARCHANGELICA ROOT 8 [hp_X]/100 mL; PINE NEEDLE OIL (PINUS SYLVESTRIS) 12 [hp_X]/100 mL; SODIUM CHLORIDE 12 [hp_X]/100 mL; ALTHAEA OFFICINALIS ROOT 8 [hp_X]/100 mL
INACTIVE INGREDIENTS: WATER; GLYCERIN; BERGAMOT OIL

Allergy Kids

Drug Facts

ACTIVE INGREDIENT

Active ingredients | Purpose
Urtica dioica [Certified Organic] 8X | Treats Hives or Other Rash-Like Eruptions
Althaea officinalis 8X | For Itching Rash-Like Symptoms
Inula helenium 8X | Expectorant, for Respiratory Issues
Angelica archangelica 8X | Remedy for Inflammation/Allergies
Pinus sylvestris 12X | Relieves Itching
Natrum muriaticum 12X | Itchy Eyes/Hay Fever Relief

Uses

for the temoirart relief of allergy and hay fever symptoms including:

- Sneezing
- Runny Nose
- Itchy Eyes, Nose, Throat

Warnings

For oral (sublingual) use.

Keep out of reach of children.

Recommended for childrenages 3 to 12.

Stop use and ask a doctorif symptoms persist for more than 3 days or worsen.

Directions

Shake well before use. For best results, use at the first sign of symptoms.

For an allergic reaction:

Place 5-10 drops under the tongue. Repeat as needed, up to every 15 minutes, until symptoms improve.

For ongoing immune support:

Use 5-10 drops under the tongue daily.

Other information

- Store in a cool, dark place
- Store upright
- Tighten cap after use to prevent oxidation

Inactive ingredients

Bergamot Oil*, Distilled Water, Glycerin* (USP)

*Certified Organic

Questions?

1-877-975-3797

forcesofnaturemedicine.com

Manufactured by: Forces of Nature, Inc.
21787 8th St East, Sonoma, CA 95476

PRINCIPAL DISPLAY PANEL - 10 ml Bottle Carton

HOMEOPATHIC
NDC #51393-5008-1

FORCES OF NATURE®

TRUSTED PLANT REMEDIES

KIDS

FOR AGES 3 - 12

Allergy

FAST MULTI-SYMPTOM RELIEF

for runny nose ,sneezing & itchy eyes

Proprietary homeopathic blend

Indoor & outdoor allergies

Non-drowsy

Organic Orange Flavor

NON
GMO
Project
VERIFIED
nongmoproject.org

USDA
ORGANGIC

10 ml (0.34 FL OZ)